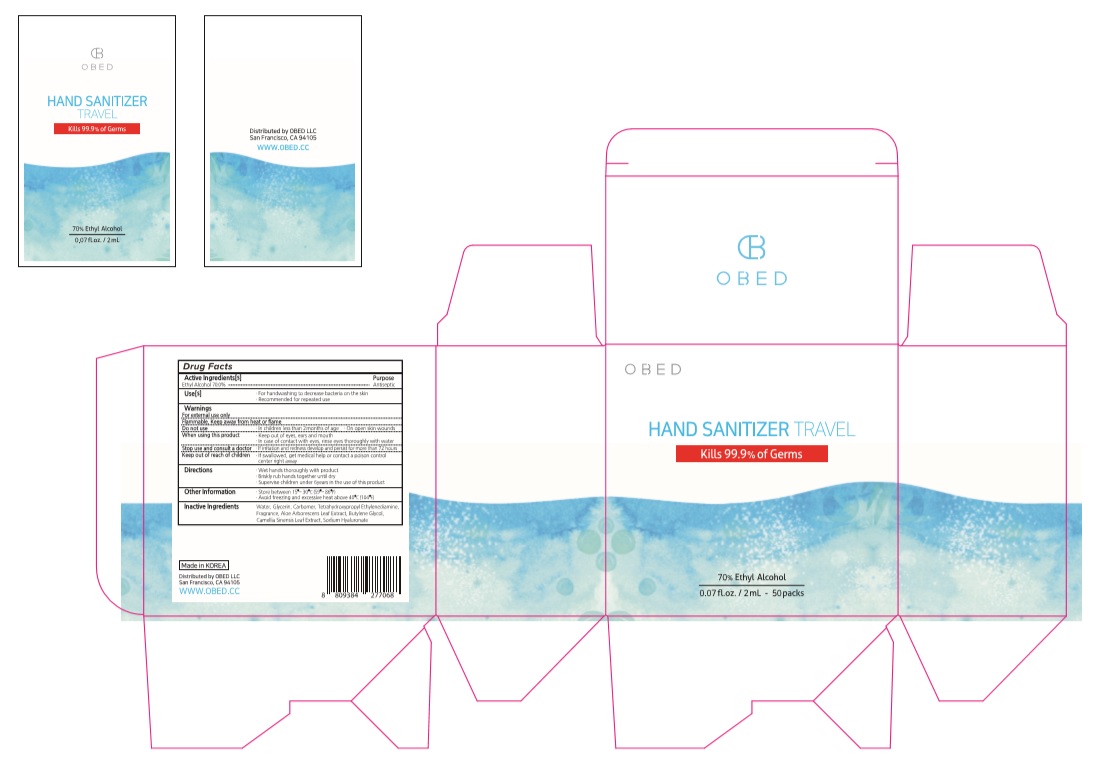 DRUG LABEL: OBED HAND SANITIZER TRAVEL
NDC: 74004-002 | Form: GEL
Manufacturer: Ester Co., Ltd.
Category: otc | Type: HUMAN OTC DRUG LABEL
Date: 20200708

ACTIVE INGREDIENTS: ALCOHOL 1.4 mL/2 mL
INACTIVE INGREDIENTS: HYALURONATE SODIUM; BUTYLENE GLYCOL; GREEN TEA LEAF; ALOE VERA LEAF; EDETOL; CARBOMER HOMOPOLYMER, UNSPECIFIED TYPE; 1,2-HEXANEDIOL; WATER; GLYCERIN

[Ester Co., Ltd.-OBED HAND SANITIZER TRAVEL]
2 mL pouch x 50 EA in box